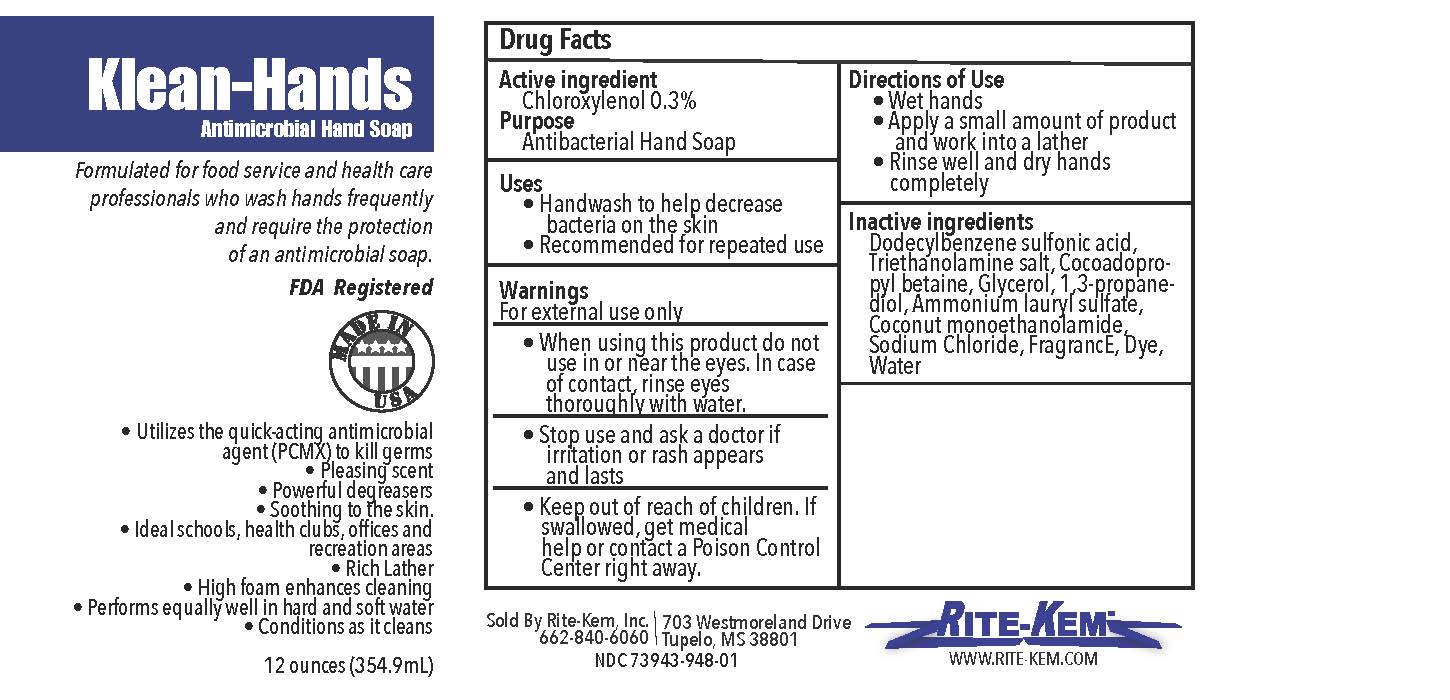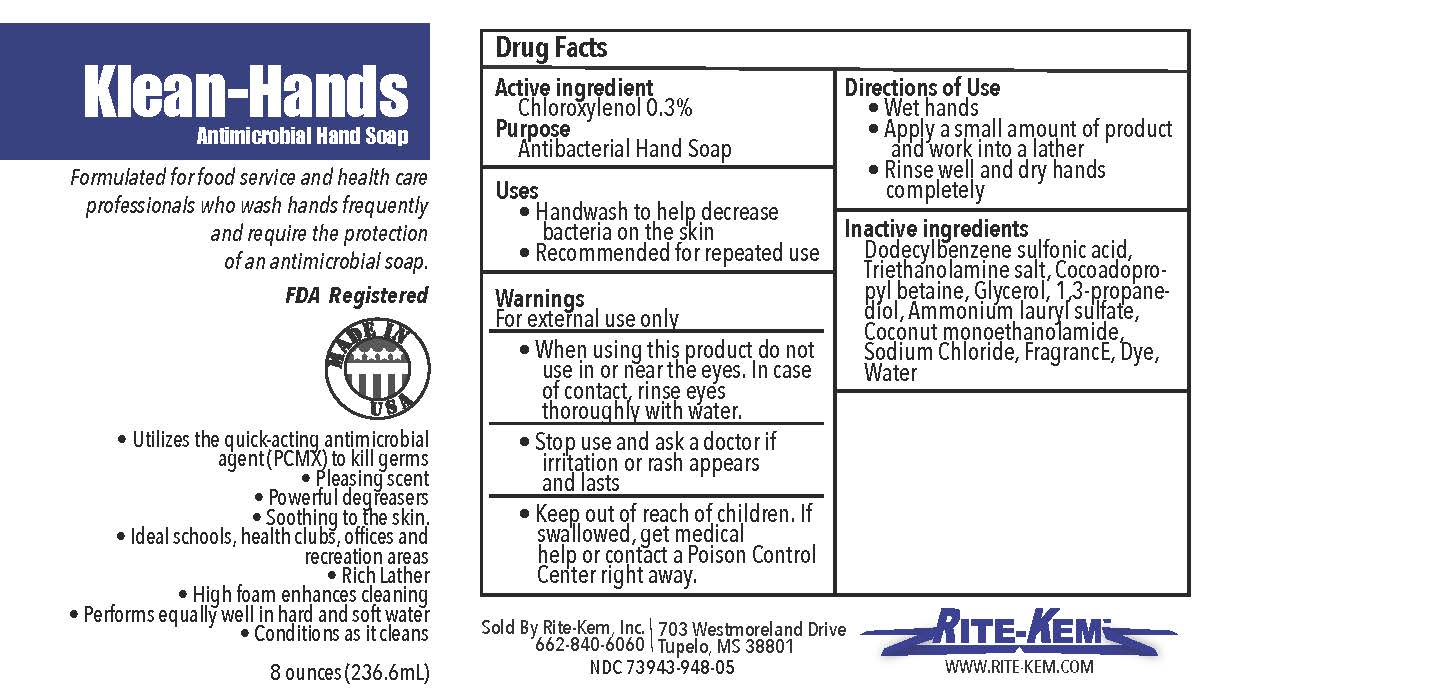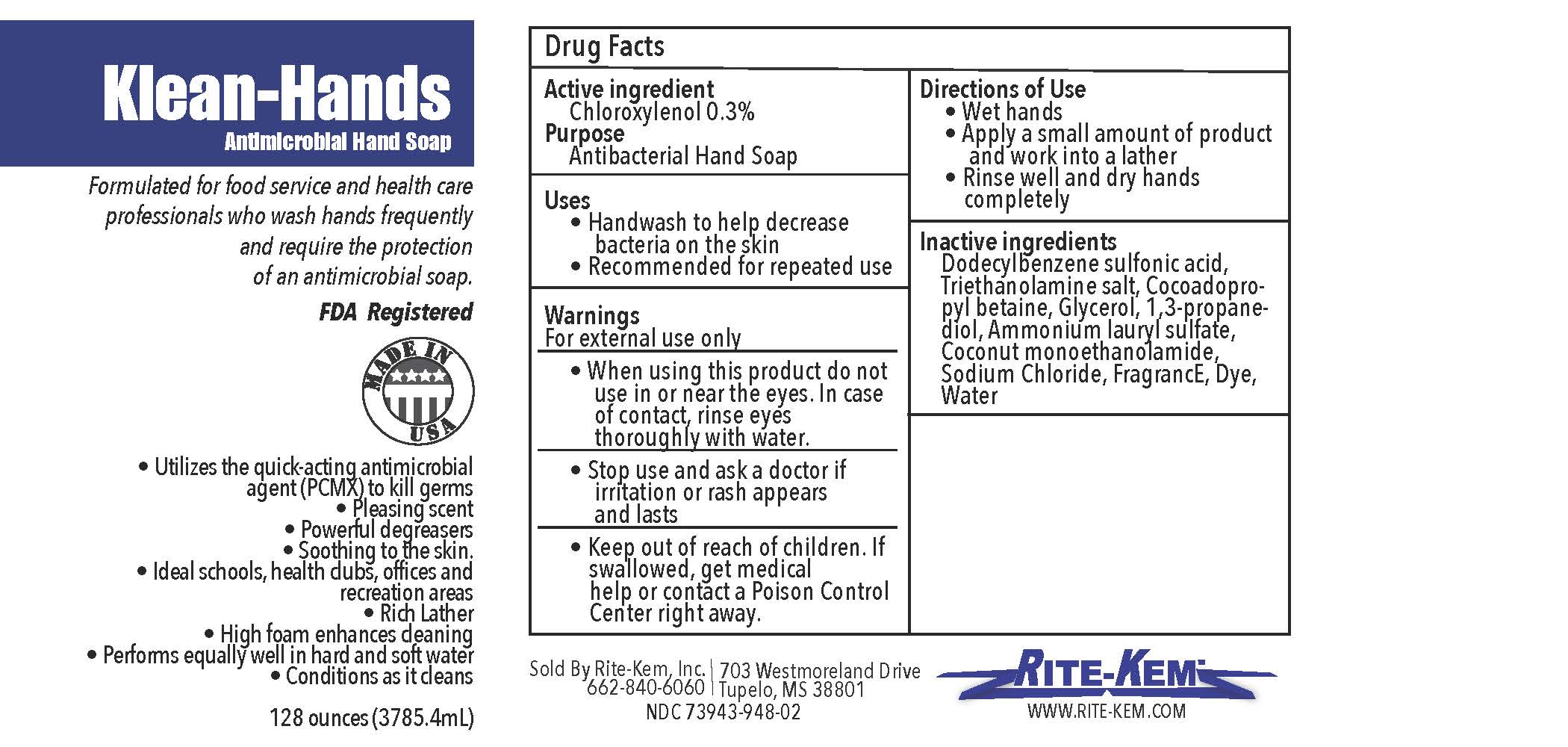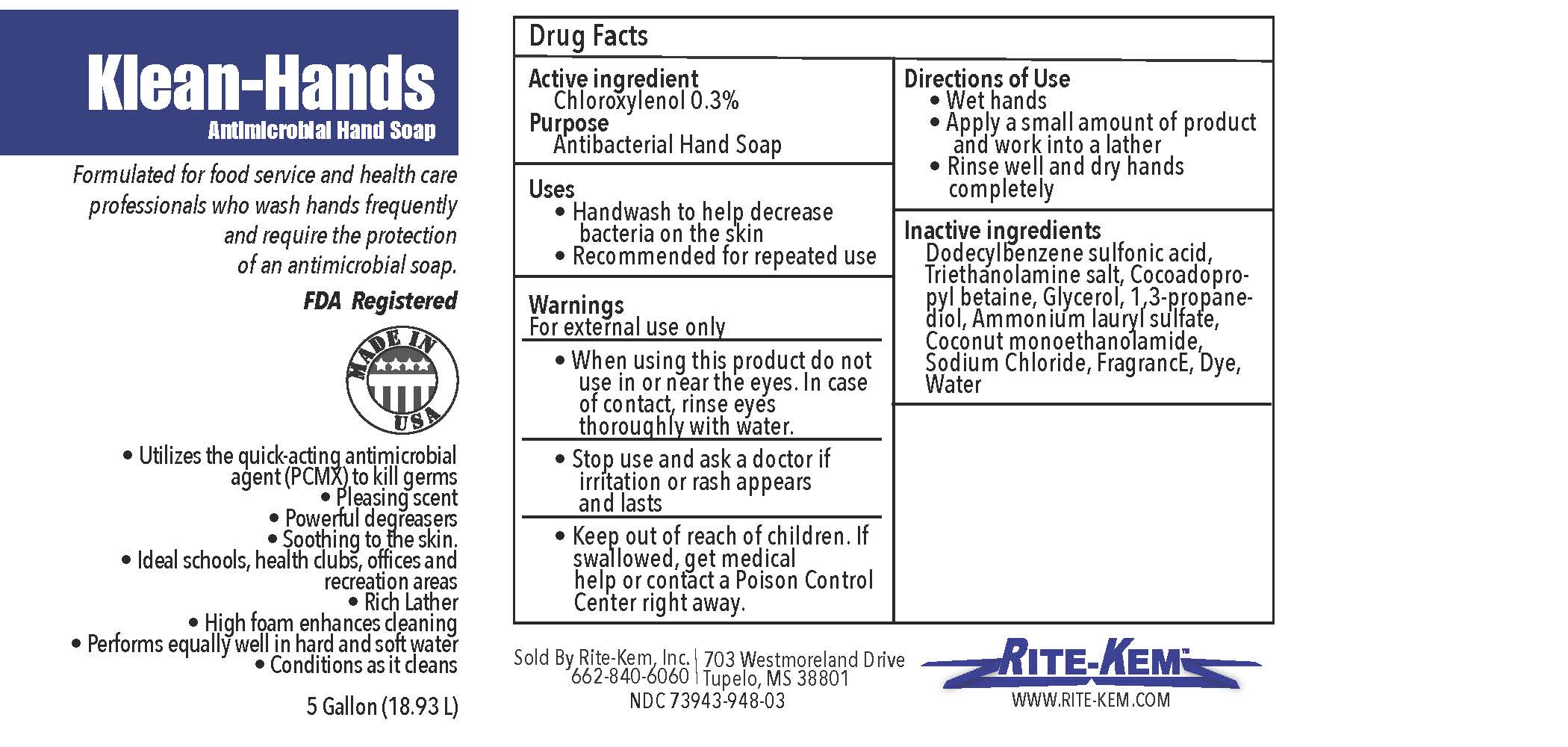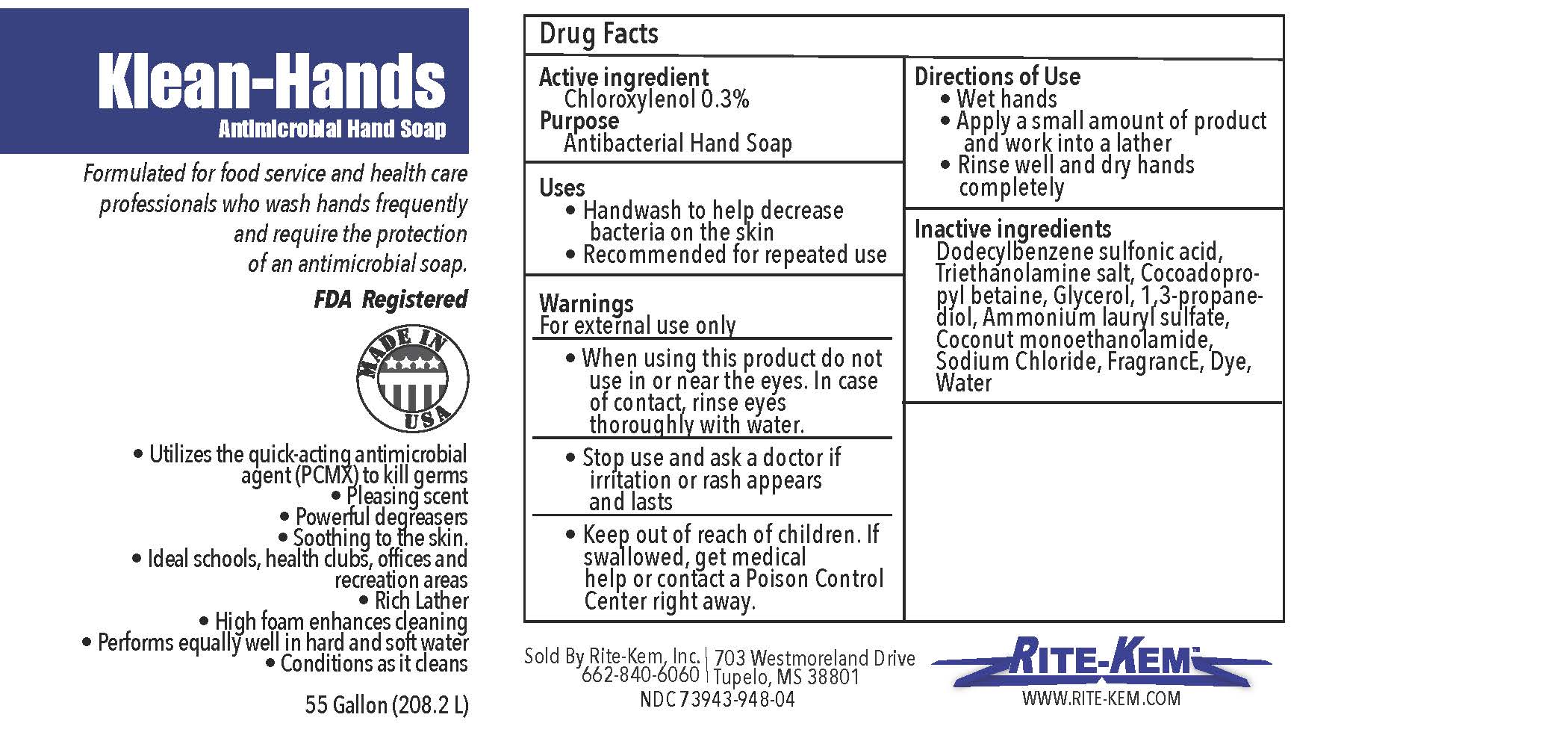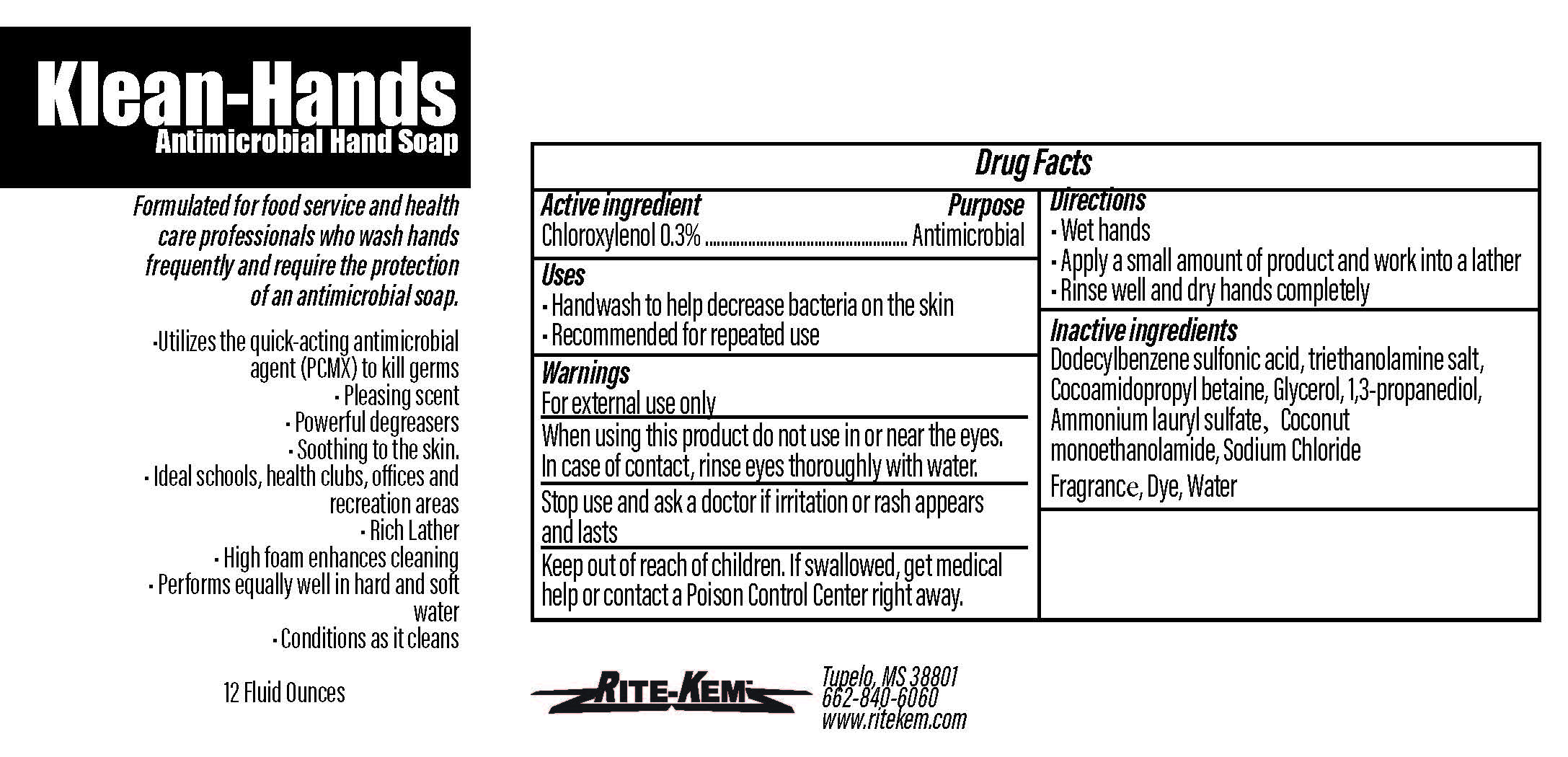 DRUG LABEL: Klean-Hands
NDC: 73943-948 | Form: LIQUID
Manufacturer: Rite-Kem Incorporated
Category: otc | Type: HUMAN OTC DRUG LABEL
Date: 20210314

ACTIVE INGREDIENTS: CHLOROXYLENOL 0.3 mg/1 mL
INACTIVE INGREDIENTS: TROLAMINE; GLYCERIN; SODIUM CHLORIDE; COCO MONOETHANOLAMIDE; LAVENDER OIL; PROPANEDIOL; AMMONIUM LAURYL SULFATE; DODECYLBENZENESULFONIC ACID; COCAMIDOPROPYL BETAINE

Antimicrobial Hand Soap

COMPONENTS

Chloroxylenol 0.3%

PURPOSE

Antimicrobial Hand Soap

INDICATIONS AND USAGE

Handwash to help decrease bacteria on the skin. Recommended for repeated use

WARNINGS

For external use only

When using this product do not use in or near the eyes. In case of contact, rinse eyes thoroughly with water.

Stop use and ask a doctor if irritation or rash appears and lasts

Keep out of reach of children. If swallowed, get medical help or contact a Poison Control Center right away.

DOSAGE AND ADMINISTRATION

Wet hands
Apply a small amount of product and work into a lather
Rinse well and dry hands completely

ACTIVE INGREDIENT

Chloroxylenol 0.3%

INACTIVE INGREDIENT

Dodecylbenzene sulfonic acid, triethanolamine salt, Cocoamidopropyl betaine, Glycerol, 1,3-propanediol, Ammonium lauryl sulfate, Coconut monoethanolamide, Sodium Chloride, Fragrance, Dye, Water

Label

Klean-Hands Antimicrobial Hand soap

Formulated for food service and health care professionals who wash hands frequently and require the protection of an antimicrobial soap.

FDA registered

Made in USA

* Utilize the quickacting antimicrobial agent (PCMX) to kill germs

* Pleasing agent

* Powerful degreasers

* Soothing to the skin

* Ideal schools, health clubs, offices and recreation areas

* Rich Lather

* High foam enhances cleaning

* Performs equally well in hand and soft water

* Conditions as it cleans

Sold by: Rite-Kem Inc., 703 Westmoreland Drive, Tupelco, MS 38801

Ph.: 662-840-6060

NDC: 73943-948-xx